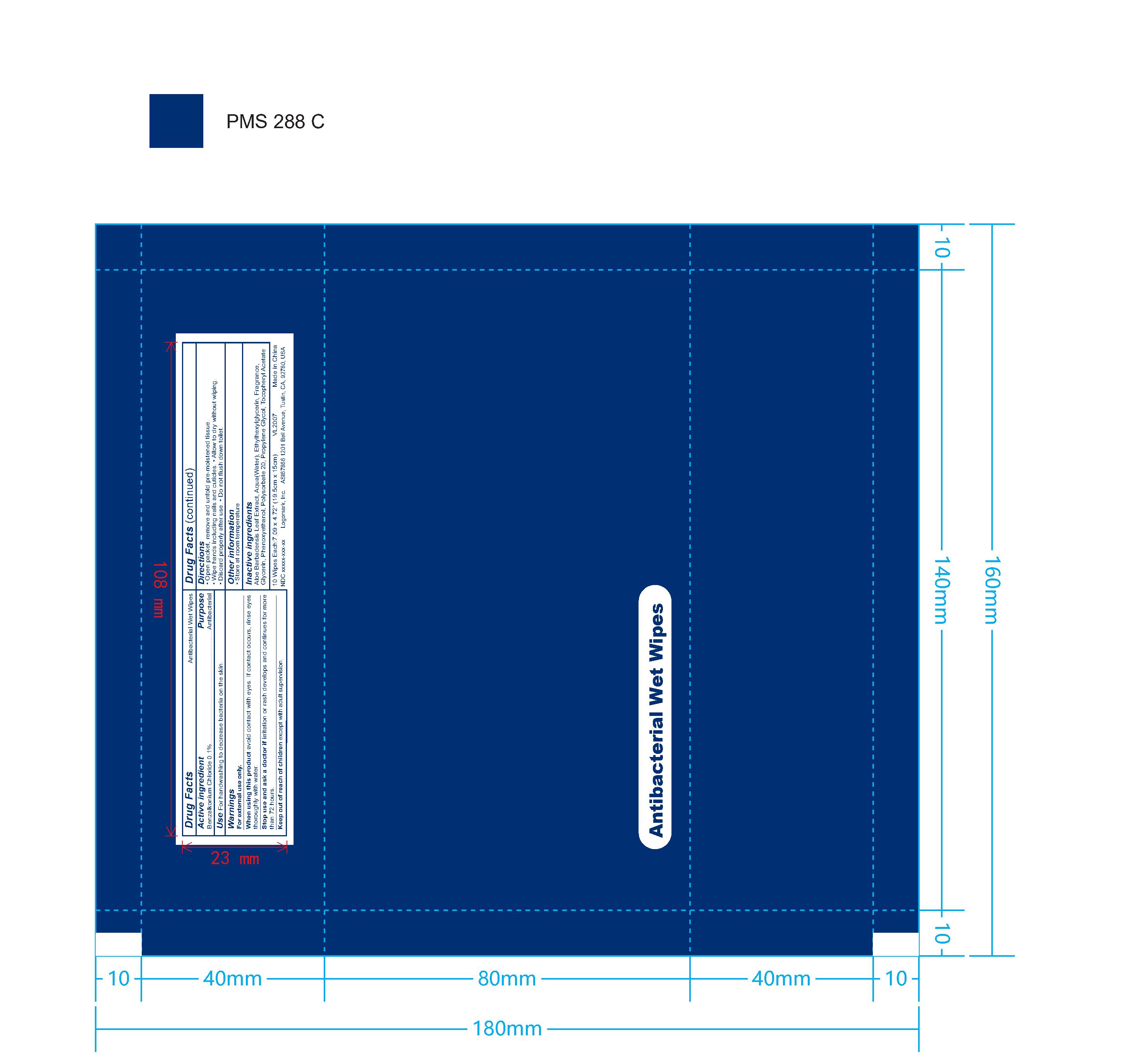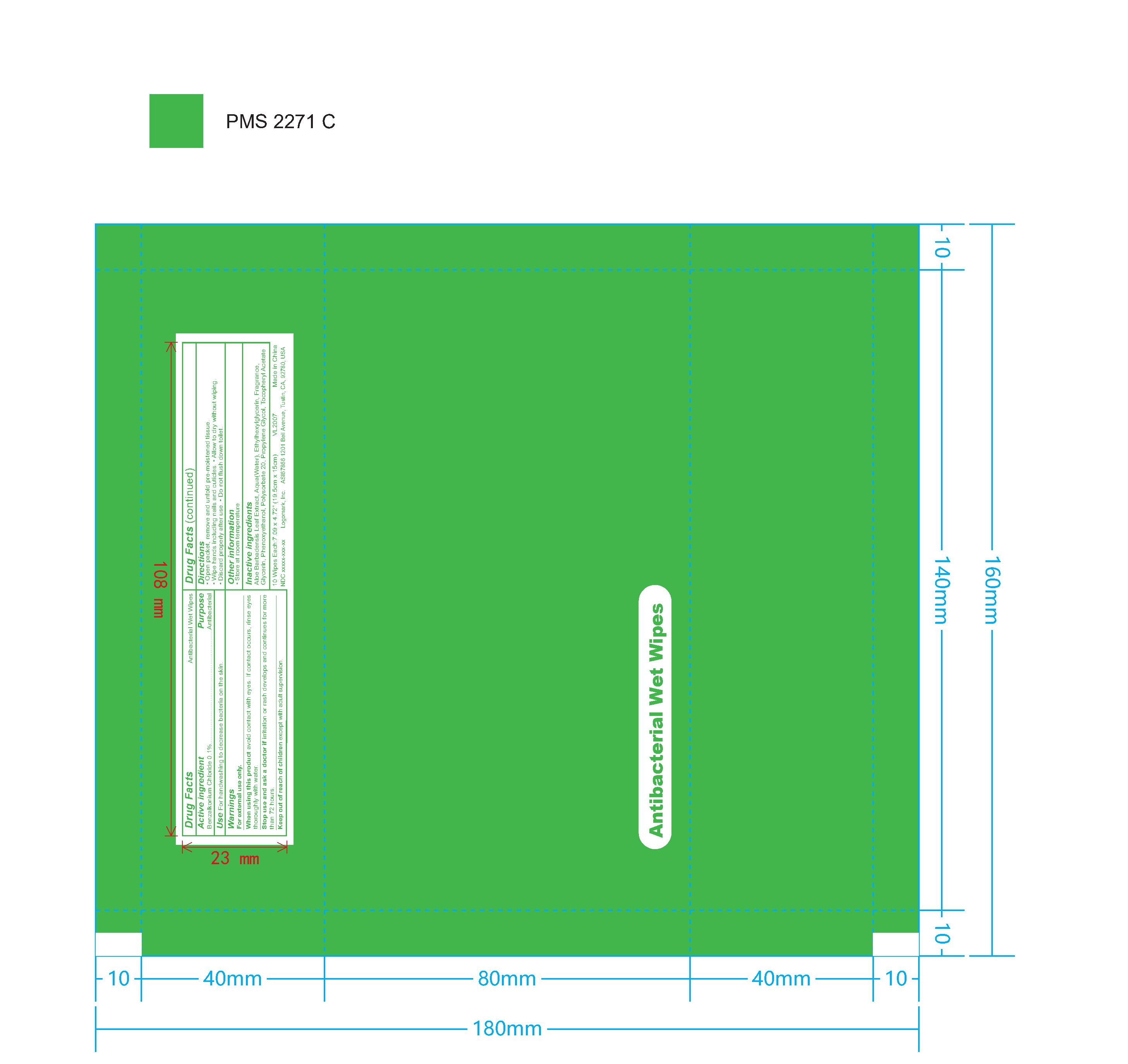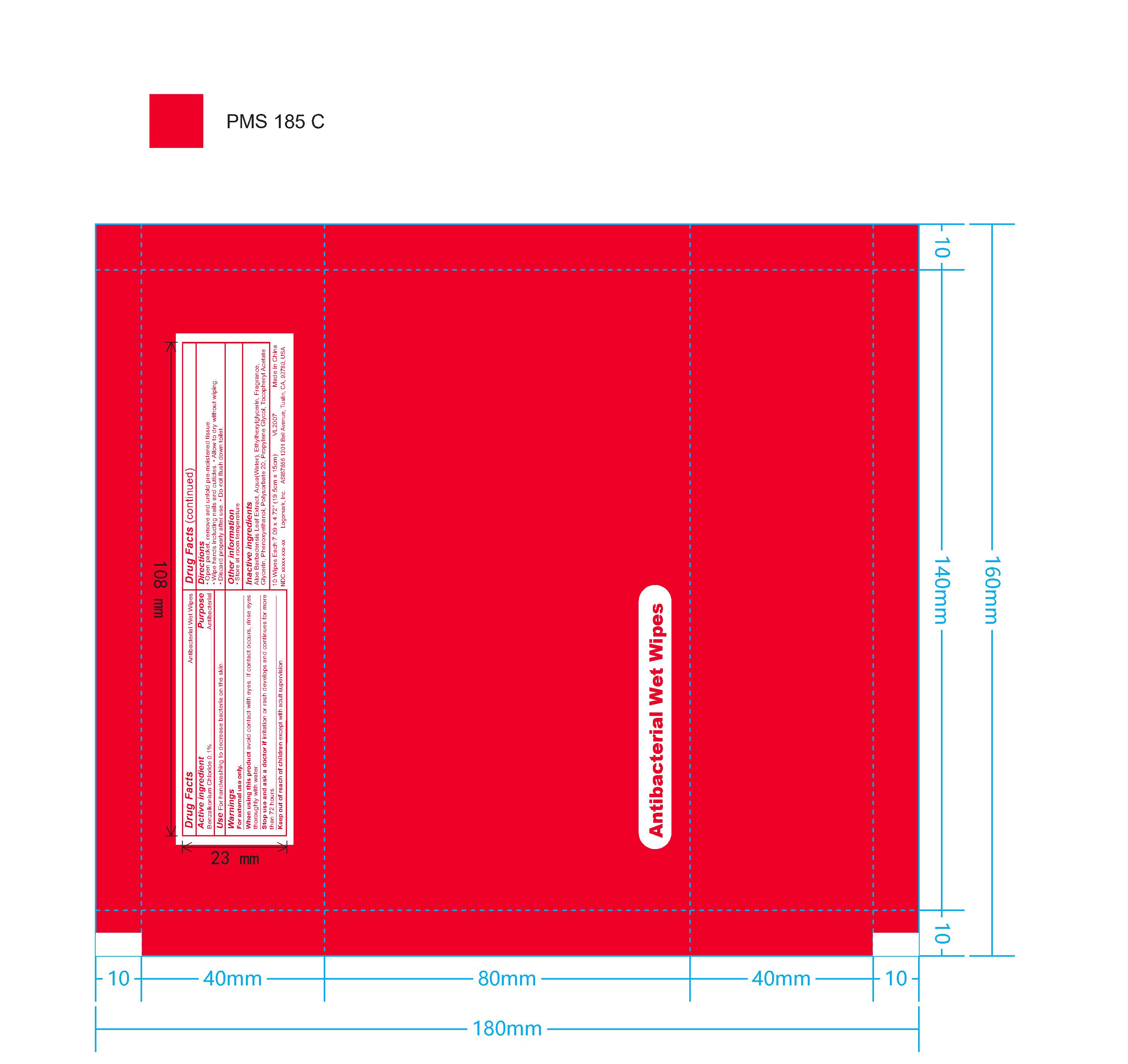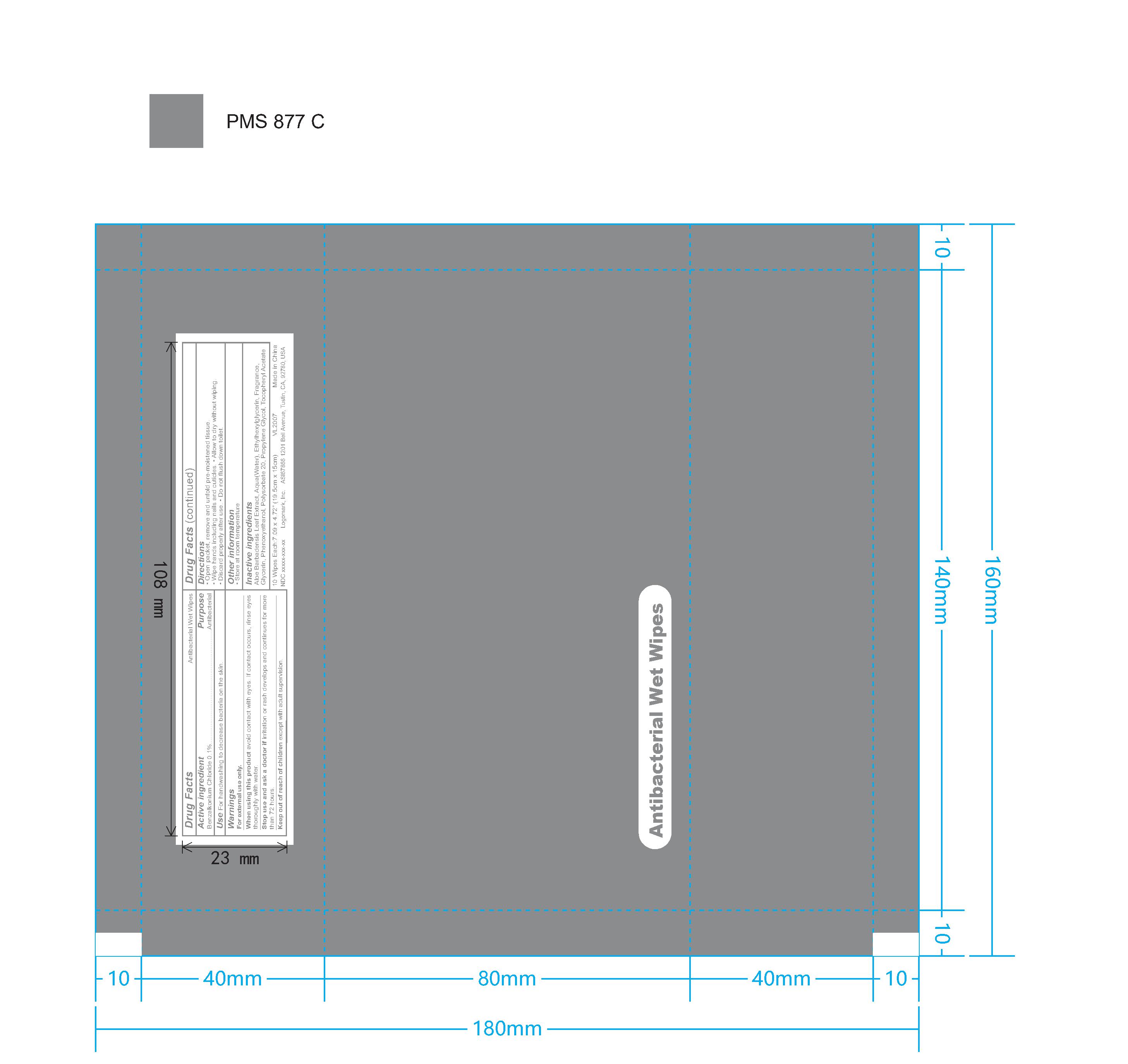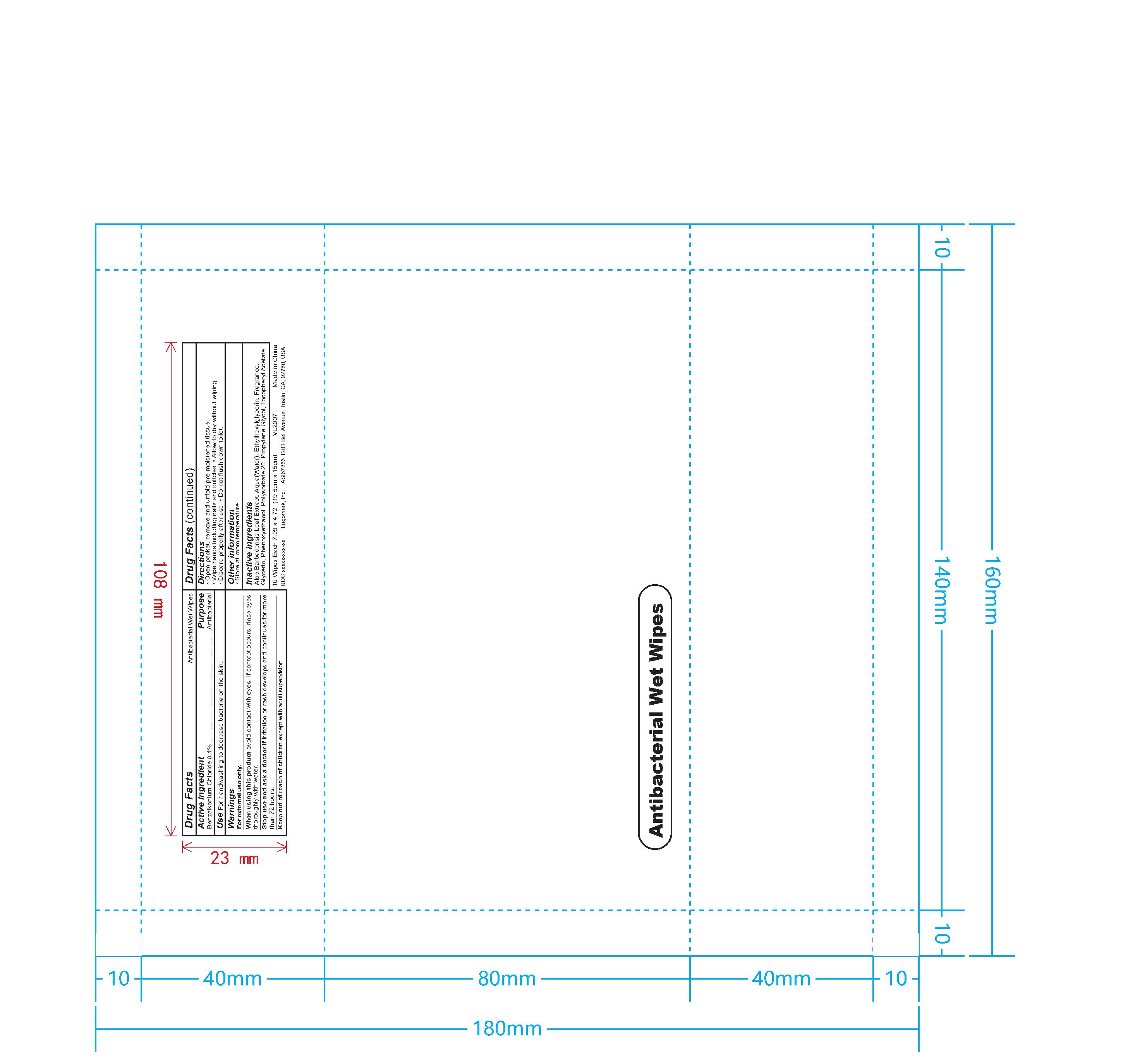 DRUG LABEL: wet wipes
NDC: 82953-048 | Form: CLOTH
Manufacturer: Cosmuses Cosmetics (Ningbo) Co., Ltd.
Category: otc | Type: HUMAN OTC DRUG LABEL
Date: 20250825

ACTIVE INGREDIENTS: BENZALKONIUM CHLORIDE 0.1 g/100 1
INACTIVE INGREDIENTS: ALOE VERA LEAF; PHENOXYETHANOL; .ALPHA.-TOCOPHEROL ACETATE, DL-; WATER; GLYCERIN; POLYSORBATE 20; ETHYLHEXYLGLYCERIN; PROPYLENE GLYCOL; FRAGRANCE 13576

Wet wipes

Drug Fact

Active Ingredient

Benzalkonium Chloride 0.10%

Purpose

Antibacterial

Uses

For handwashing to decrease bacteria on the skin,

Warning

For external use only.

When using this product avoid contact with eyes. If contact occurs, rinse eyes thoroughtly with water.

Stop use and ask a doctor if irritation or redness develop and continues for more than 72 hours.

Keep out of reach of children except with adult supervision.

Directions

- Open packet, remove and unfold pre-moistened tissue
- Wipe hands including nails and cuticles.
- Allow to dry without wiping
- Discard properly after use.
- Do not flush down toilet.

other information

- Store at room temperature.

Inactive Ingredients

Aloe Barbadensis Leaf Extract, Aqua(water), Ethylhexylglycerin, Fragrance, Glycerin, Phenoxyethanol, Polysorbate 20, Propylene Glycol, Tocopheryl Acetate.